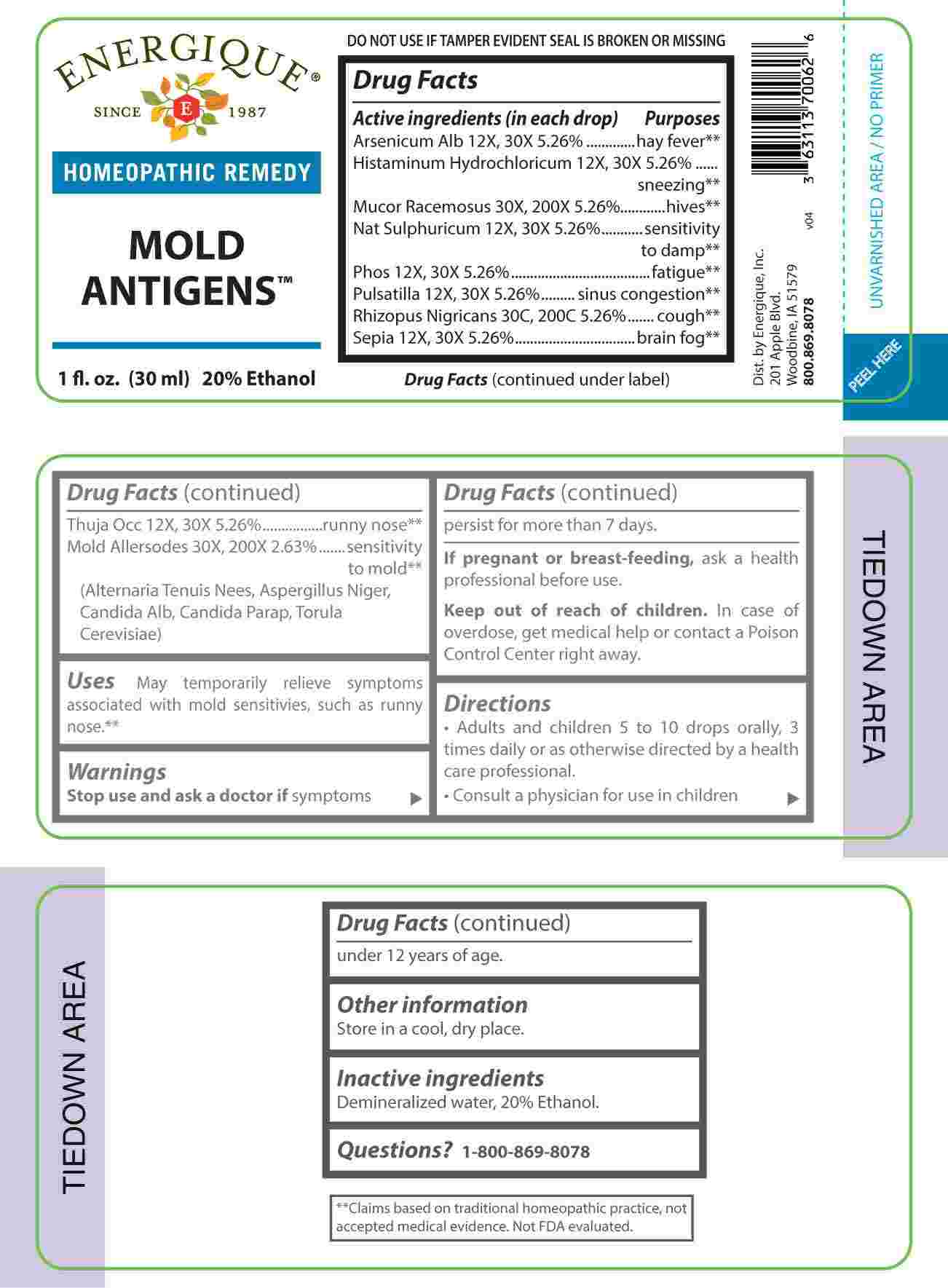 DRUG LABEL: Mold Antigens
NDC: 44911-0702 | Form: LIQUID
Manufacturer: Energique, Inc.
Category: homeopathic | Type: HUMAN OTC DRUG LABEL
Date: 20231222

ACTIVE INGREDIENTS: ARSENIC TRIOXIDE 12 [hp_X]/1 mL; HISTAMINE DIHYDROCHLORIDE 12 [hp_X]/1 mL; SODIUM SULFATE 12 [hp_X]/1 mL; PHOSPHORUS 12 [hp_X]/1 mL; PULSATILLA PRATENSIS WHOLE 12 [hp_X]/1 mL; SEPIA OFFICINALIS JUICE 12 [hp_X]/1 mL; THUJA OCCIDENTALIS LEAFY TWIG 12 [hp_X]/1 mL; ALTERNARIA ALTERNATA 30 [hp_X]/1 mL; ASPERGILLUS NIGER VAR. NIGER 30 [hp_X]/1 mL; CANDIDA ALBICANS 30 [hp_X]/1 mL; CANDIDA PARAPSILOSIS 30 [hp_X]/1 mL; SACCHAROMYCES CEREVISIAE 30 [hp_X]/1 mL; MUCOR RACEMOSUS 30 [hp_X]/1 mL; RHIZOPUS STOLONIFER 30 [hp_C]/1 mL
INACTIVE INGREDIENTS: WATER; ALCOHOL

DRUG FACTS:

ACTIVE INGREDIENTS:

(in each drop): Arsenicum Album 12X, 30X 5.26%, Histaminum Hydrochloricum 12X, 30X 5.26%, Mucor Racemosus 30X, 200X 5.26%, Natrum Sulphuricum 12X, 30X 5.26%, Phosphorus 12X, 30X 5.26%, Pulsatilla 12X, 30X 5.26%, Rhizopus Nigricans 30C, 200C 5.26%, Sepia 12X, 30X 5.26%, Thuja Occidentalis 12X, 30X 5.26%, Alternaria Tenuis Nees 30X, 200X 2.63%, Aspergillus Niger 30X, 200X 2.63%, Candida Albicans 30X, 200X 2.63%, Candida Parapsilosis 30X, 200X 2.63%, Torula Cerevisiae 30X, 200X 2.63%.

PURPOSE:

Arsenicum Album – hay fever,** Histaminum Hydrochloricum - sneezing,** Mucor Racemosus - hives,** Natrum Sulphuricum – sensitivity to damp,** Phosphorus - fatigue,** Pulsatilla – sinus congestion,** Rhizopus Nigricans - cough,** Sepia – brain fog,** Thuja Occidentalis – runny nose,** Alternaria Tenuis Nees – sensitivity to mold,** Aspergillus Niger - sensitivity to mold,** Candida Albicans - sensitivity to mold,** Candida Parapsilosis - sensitivity to mold,** Torula Cerevisiae - sensitivity to mold.****Claims based on traditional homeopathic practice, not accepted medical evidence. Not FDA evaluated.

USES:

May temporarily relieve symptoms associated with mold sensitivies, such as runny nose.**

**Claims based on traditional homeopathic practice, not accepted medical evidence. Not FDA evaluated.

WARNINGS:

Stop use and ask a doctor if symptoms persist for more than 7 days.

If pregnant or breast-feeding, ask a health professional before use.

Keep out of reach of children. In case of overdose, get medical help or contact a Poison Control Center right away.

DO NOT USE IF TAMPER EVIDENT SEAL IS BROKEN OR MISSING

KEEP OUT OF REACH OF CHILDREN:

In case of overdose, get medical help or contact a Poison Control Center right away.

DIRECTIONS:

• Adults and children 5 to 10 drops orally, 3 times daily or as otherwise directed by a health care professional.• Consult a physician for use in children under 12 years of age.

ACTIVE INGREDIENTS:

Demineralized water, 20% Ethanol.

QUESTIONS:

Dist. by Energique, Inc.

201 Apple Blvd.

Woodbine, IA 51579

800.869.8078

PACKAGE LABEL DISPLAY:

ENERGIQUE

SINCE 1987

HOMEOPATHIC REMEDY

MOLD

ANTIGENS

1 fl. oz. (30 ml)